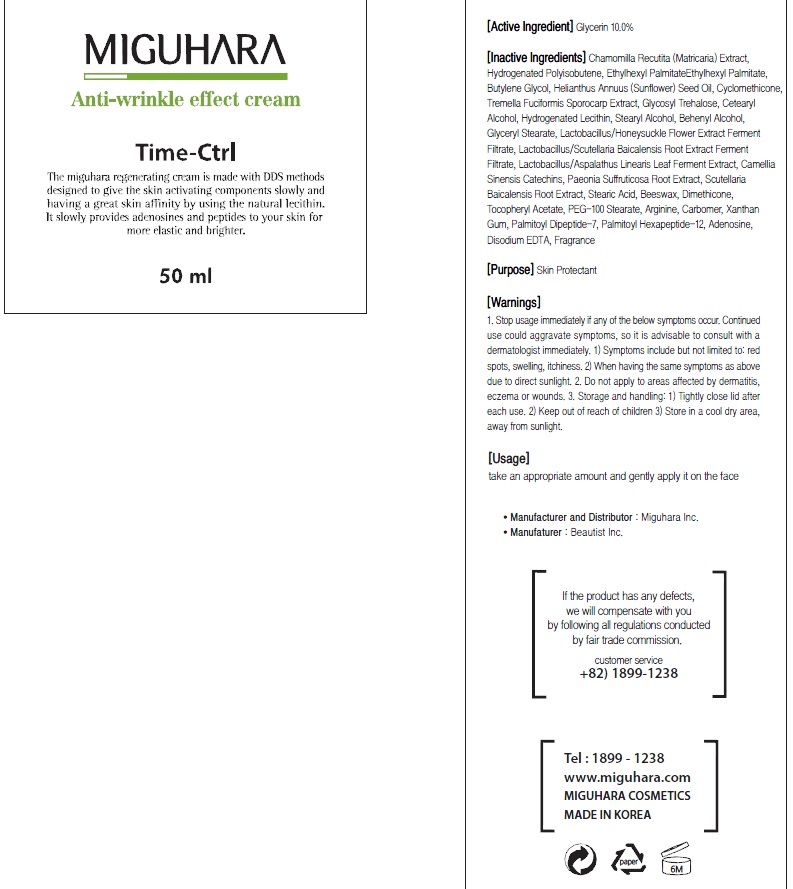 DRUG LABEL: Anti Wrinkle Effect Eye
NDC: 70380-110 | Form: CREAM
Manufacturer: MIGUHARA
Category: otc | Type: HUMAN OTC DRUG LABEL
Date: 20160218

ACTIVE INGREDIENTS: Glycerin 1.2 g/20 mL
INACTIVE INGREDIENTS: GREEN TEA LEAF; HYALURONATE SODIUM

ACTIVE INGREDIENT

Active Ingredient: Glycerin 6.0%

INACTIVE INGREDIENT

Inactive Ingredients: Camellia Sinensis Leaf Extract, Sodium Hyaluronate, Camellia Japonica Seed Oil, Helianthus Annuus (Sunflower) Seed Oil, Ethylhexyl Palmitate , Chamomilla Recutita (Matricaria) Leaf Extract, Glycyrrhiza Glabra (Licorice) Root Extract, Centella Asiatica Extract, Glycine Max (Soybean) Seed Extract, Eclipta Prostrata Extract, Rehmannia Chinensis Root Extract, Artemisia Princeps Leaf Extract, Portulaca Oleracea Extract, Lactobacillus/Aspalathus Linearis Leaf Ferment Extract, Lactobacillus/Honeysuckle Flower Extract Ferment Filtrate, Bifida Ferment Lysate, Tremella Fuciformis Sporocarp Extract, Steareth-21, Steareth-2, Propylene Glycol, Butylene Glycol, Lecithin, Cetearyl Alcohol, Lonicera Japonica (Honeysuckle) Flower Extract , Zanthoxylum Piperitum Fruit Extract, Pulsatilla Koreana Extract, Citrus Paradisi (Grapefruit) Fruit Extract, Hydrolyzed Collagen, Dioscorea Opposita (Wild Yam) Root Extract, Stearic Acid, Microcrystalline Wax, Beeswax, Butyrospermum Parkii (Shea) Butter, Acetyl Hexapeptide-8, Arginine, Carbomer, Xanthan Gum, Tocopheryl Acetate, Adenosine, Disodium EDTA, Citrus Aurantium Dulcis (Orange) Oil, Aniba Rosaeodora (Rosewood) Wood Oil, Lavandula Angustifolia (Lavender) Oil, Rosmarinus Officinalis (Rosemary) Leaf Oil, Foeniculum Vulgare (Fennel) Oil, Citrus Limon (Lemon) Fruit Oil

PURPOSE

Purpose: Skin Protectant

WARNINGS

1. Stop usage immediately if any of the below symptoms occur. Continued use could aggravate symptoms, so it is advisable to consult with a dermatologist immediately. 1) Symptoms include but not limited to: red spots, swelling, itchiness. 2) When having the same symptoms as above due to direct sunlight. 2. Do not apply to areas affected by dermatitis, eczema or wounds. 3. Storage and handling: 1) Tightly close lid after each use. 2 Keep out of reach of children 3) Store in a cool dry area, away from sunlight 4. Be aware not to get into eye

Usage

Usage: Take an appropriate amount and gently apply it on the eye area.

Usage

Usage: Take an appropriate amount and gently apply it on the eye area.

KEEP OUT OF REACH OF CHILDREN